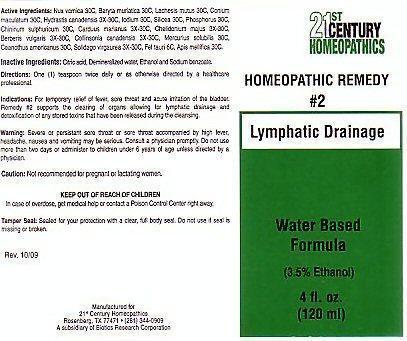 DRUG LABEL: CENTURY 21 LYMPHATIC DRAINAGE
NDC: 63972-002 | Form: LIQUID
Manufacturer: 21st Century Homeopathics, Inc
Category: homeopathic | Type: HUMAN OTC DRUG LABEL
Date: 20100101

ACTIVE INGREDIENTS: STRYCHNOS NUX-VOMICA SEED 30 [hp_C]/5 mL; BARIUM CHLORIDE DIHYDRATE 30 [hp_C]/5 mL; LACHESIS MUTA VENOM 30 [hp_C]/5 mL; CONIUM MACULATUM FLOWERING TOP 30 [hp_C]/5 mL; GOLDENSEAL 30 [hp_C]/5 mL; IODINE 30 [hp_C]/5 mL; SILICON DIOXIDE 30 [hp_C]/5 mL; PHOSPHORUS 30 [hp_C]/5 mL; QUININE SULFATE 30 [hp_C]/5 mL; SILYBUM MARIANUM SEED 30 [hp_C]/5 mL; CHELIDONIUM MAJUS 30 [hp_C]/5 mL; BERBERIS VULGARIS ROOT BARK 30 [hp_C]/5 mL; COLLINSONIA CANADENSIS ROOT 30 [hp_C]/5 mL; MERCURIUS SOLUBILIS 30 [hp_C]/5 mL; CEANOTHUS AMERICANUS LEAF 30 [hp_C]/5 mL; SOLIDAGO VIRGAUREA FLOWERING TOP 30 [hp_C]/5 mL; BOS TAURUS BILE 6 [hp_C]/5 mL; APIS MELLIFERA 30 [hp_C]/5 mL
INACTIVE INGREDIENTS: CITRIC ACID MONOHYDRATE; WATER; ALCOHOL; SODIUM BENZOATE

Active Ingredients

Active Ingredients: Nux vomica 30C, Baryta muriatica 30C, Lachesis mutus 30 C, Conium maculatum 30C, Hydrastis canadensis 3X-30C, Iodium 30C, Silicea 30C, Phosphorus 30C, Chininum sulphuricum 30C, Carduus marianus 3X-30C, Chelidonium majus 3X-30C, Berberis vulgaris 3X-30C, Collinsonia candenis 3X-30C, Mercurius solubilis 30C, Ceanothus anericanus 30C, Solidago virgaurea 3X-30C, Fel tari 6C, Apis mellifica 30C

Inactive Ingredients

Inactive Ingredients: Citric acid, demineralized water, Ethanol and Sodium benzoate.

Directions For Use

Directions: One (1) teaspoon twice daily or as directed by a healthcare professional.

Indications

Indications: For temporary relief of fever, sore throat and acute irritation of the bladder. Remedy #2 supports the clearing of organs allowing for lymphatic drainage and detoxification of any stored toxins that have been released during the cleansing.

Keep Out Of Reach Of Children

In case of overdose, get medical help or contact a Poison Control Center right away.

Purpose

Lymphatic Drainage

Warnings

Warning: Severe or persistant sore throat or sore throat accompanied by high fever, headache, nausea and vomiting may be serious. Consult a physician promptly. Do not use more than two days or administer to children under 6 years of age unless directed by a physician.
Caution: Not recommended for pregnant or lactating women

Product Label

21st CENTURY HOMEOPATHICS
HOMEOPATHIC REMEDY #2 Lymphatic Drainage
Water based Formula (3.5% Ethanol) 4 fl. oz. (120ml)
Tamper Seal: Sealed for your protection with a clear, full body seal. Do not use if seal is missing or broken.
Rev 10/09 Manufactured for 21st Century Homeopathics Rosenburg, Tx 77471 (281) 344-0909 A subsidiary of Biotics Research Corporation